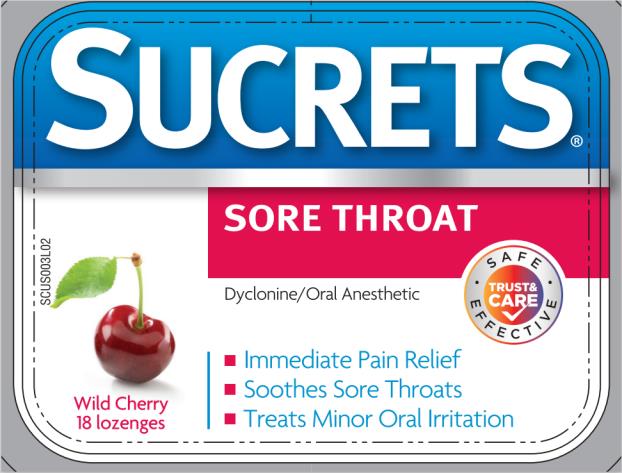 DRUG LABEL: Sucrets Sore Throat Wild Cherry
NDC: 63736-560 | Form: LOZENGE
Manufacturer: Insight Pharmaceuticals LLC
Category: otc | Type: HUMAN OTC DRUG LABEL
Date: 20240320

ACTIVE INGREDIENTS: DYCLONINE HYDROCHLORIDE 2 mg/1 1
INACTIVE INGREDIENTS: CORN SYRUP; FD&C BLUE NO. 1; FD&C RED NO. 40; MENTHOL; PROPYLENE GLYCOL; SUCROSE; TARTARIC ACID; WATER

Sucrets Sore Throat Wild Cherry

Drug Facts

Active ingredients (per lozenge)

Dyclonine hydrochloride, 2.0 mg

Purpose

Oral anesthetic

Uses

For temporary relief of occasional:

- minor irritation
- pain
- sore mouth
- sore throat

Warnings

Sore through warning: if sore throat is severe, persists for more than 2 days, is accompanied by fever, headache, rash, swelling, nausea, or vomiting, consult a doctor promptly.

Stop use and ask a doctor if

- sore mouth symptoms do not improve in 7 days
- irritation, pain or redness persists or worsens
- swelling, rash, or fever develops

If pregnant or breast-feeding,

ask a health professional before use.

Keep out of reach of children.

In case of overdose, get medical help or contact a Poison Control Center (1-800-222-1222) right away.

Directions

- do not use more than directed
- adults and children 4 years of age and older: allow lozenge to dissolve slowly in mouth. May be repeated every 2 hours as needed or as directed by a dentist or doctor.
- children under 4 years of age: ask a dentist or doctor

Other information

- store between 15°-30°C (59°-86°F)
- use only if lozenge blister seals are unbroken

Inactive ingredients

corn syrup, FD&C blue no 1, FD&C red no 40, flavor, menthol, propylene glycol, sucrose, tartaric acid, water

PRINCIPAL DISPLAY PANEL

Sucrets
Dyclonine/Oral Anesthetic
Wild Cherry
18 lozenges